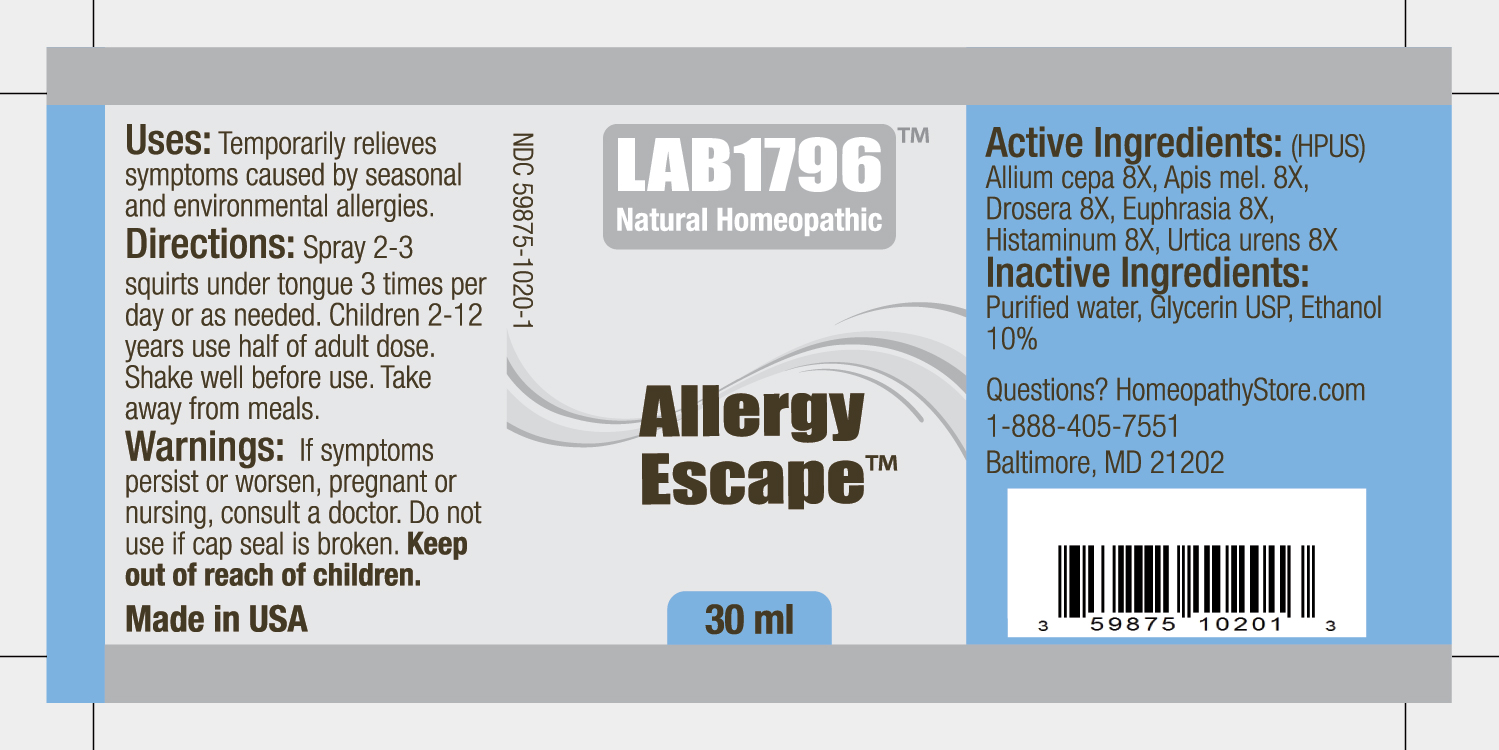 DRUG LABEL: Lab1796 Allergy Escape
NDC: 59875-1020 | Form: SPRAY
Manufacturer: HomeopathyStore.com
Category: homeopathic | Type: HUMAN OTC DRUG LABEL
Date: 20111001

ACTIVE INGREDIENTS: ONION 8 [hp_X]/1 mL; APIS MELLIFERA 8 [hp_X]/1 mL; DROSERA ROTUNDIFOLIA 8 [hp_X]/1 mL; EUPHRASIA STRICTA 8 [hp_X]/1 mL; HISTAMINE DIHYDROCHLORIDE 8 [hp_X]/1 mL; URTICA URENS 8 [hp_X]/1 mL
INACTIVE INGREDIENTS: WATER; GLYCERIN; ALCOHOL

Allergy Escape

Uses:

Temporarily relieves symptoms caused by seasonal and environmental allergies.

Directions:

DOSAGE AND ADMINISTRATION

Spray 2-3 squirts under tongue 3 times per day or as needed. Children 2-12 years use half of adult dose. Shake well before use. Take away from meals.

Warnings:

If symptoms persist or worsen, pregnant or nursing, consult a doctor. Do not use if cap seal is broken.

Keep out of reach of children.

Active Ingredients:

(HPUS) Allium cepa 8X, Apis mel. 8X, Drosera 8X, Euphrasia 8X, Histaminum 8X, Urtica urens 8X

Inactive Ingredients:

Purified water, Glycerin USP, Ethanol 10%